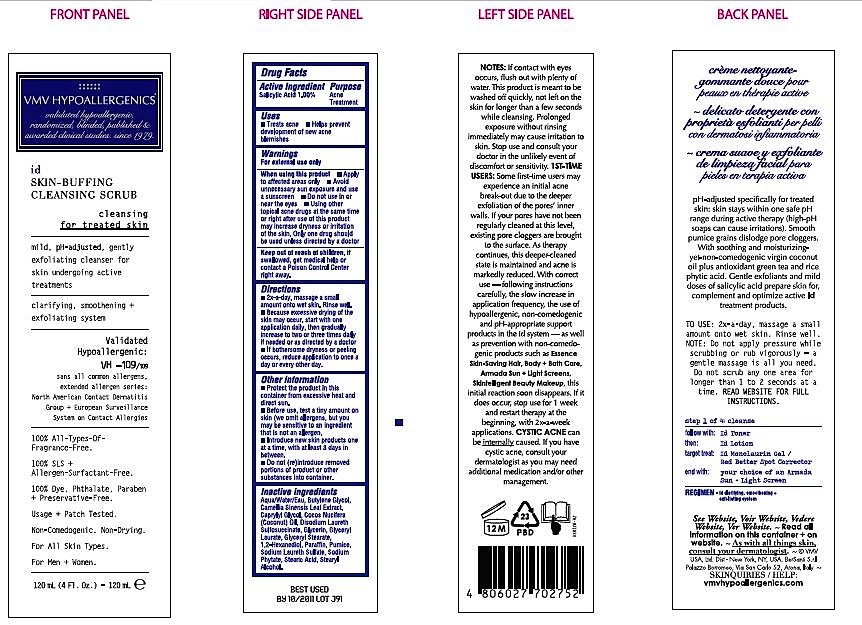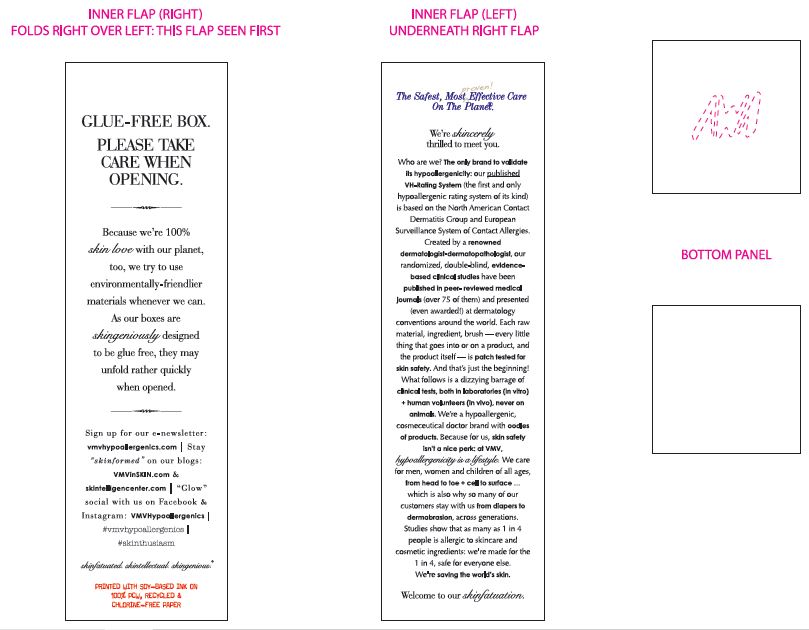 DRUG LABEL: VMV HYPOALLERGENICS ID SKIN-BUFFING CLEANSING SCRUB
NDC: 69774-551 | Form: EMULSION
Manufacturer: SKIN SCIENCES LABORATORY INC.
Category: otc | Type: HUMAN OTC DRUG LABEL
Date: 20170411

ACTIVE INGREDIENTS: SALICYLIC ACID 1.2 g/120 mL
INACTIVE INGREDIENTS: 1,2-HEXANEDIOL; GLYCERIN; 12-(9-ANTHROYLOXY)STEARIC ACID; GLYCERYL LAURATE; BUTYLENE GLYCOL; CAPRYLYL GLYCOL; DISODIUM LAURETH SULFOSUCCINATE; STEARYL ALCOHOL; WATER; SODIUM LAURETH SULFATE; PARAFFIN; GLYCERYL MONOSTEARATE; PHYTATE SODIUM

VMV Hypoallergenics ID Skin Buffing Cleansing Scrub

Active Ingredient
Salicylic Acid 1.00%

Purpose
Acne Treatment

Warnings
For external use only

When using this product

- Apply to affected areas only
- Avoid unnecessary sun exposure and use a sunscreen
- Do not use in or near the eyes
- Using other topical acne drugs at the same time
or right after use of this product
may increase dryness or irritation of the skin.
Only one drug should be used unless directed by a doctor

Keep out of reach of children,

if swallowed, get medical help or contact a Poison Control Center right away.

Directions
- 2x-a-day, massage a small
amount onto wet skin. Rinse well.
- Because excessive drying of the
skin may occur, start with one
application daily, then gradually
increase to two or three times daily
if needed or as directed by a doctor
- If bothersome dryness or peeling occurs,
reduce application to once a day or every other day.

Other information

- Protect the product in this container from excessive heat and direct sun.
- Before use, test a tiny amount on skin (we omit allergens, but you may be sensitive
to an ingredient that is not an allergen.
- Introduce new skin products one at a time, with at least 3 days in between.
- Do not (re)introduce removed portions of product or other substances into container.

Inactive ingredients
Aqua/Water/Eau, Butylene Glycol,
Camellia Sinensis Leaf Extract,
Caprylyl Glycol, Cocos Nucifera (Coconut) Oil
Disodium Laureth Sulfosuccinate, Glycerin, Glyceryl Laurate,
Glyceryl Stearate, 1,2-Hexanediol, Paraffin, Pumice
Sodium Laureth Sulfate, Sodium Phytate, Stearic Acid, Stearyl Alcohol

OTHER SAFETY INFORMATION

Notes: If contact with eyes
occurs, flush out with plenty of
water. This product is meant to be washed off quickly, not left on the
skin for longer than a few seconds
while cleansing. Prolonged
exposure without rinsing
immediately may cause irritation to
skin. Stop use and consult your
doctor in the unlikely event of
discomfort or sensitivity. 1ST-TIME
USERS: Some first-time users may
experience an initial acne
break-out due to the deeper
exfoliation of the pores' inner
walls. If your pores have not been
regularly cleaned at this level,
existing pore cloggers are brought
to the surface. As therapy
continues, this deeper-cleaned
state is maintained and acne is
markedly reduced. With correct
use - following instructions
carefully, the slow increase in
application frequency, the use of
hypoallergenic, non-comedogenic
and pH-appropriate support
products in the Id system - as well
as prevention with non-comedo-
genic products such as Essence
Skin-Saving Hair, Body + Bath Care,
Armada Sun + Light Screens,
Skintelligent Beauty Makeup, this
initial reaction soon disappears. If it
does occur, stop use for 1 week
and restart therapy at the
beginning, with 2x-a-week
applications. CYSTIC ACNE can
be internally caused. If you have
cystic acne, consult your
dermatologist as you may need
additional medication and/or other
management.

Purpose
Acne Treatment

Uses
- Treats acne
- Helps prevent development of new acne blemishes

PACKAGE LABEL

id
SKIN-BUFFING
CLEANSING SCRUB

cleansing
for treated skin

mild, pH-adjusted, gently
exfoliating cleanser for
skin undergoing active
treatments

clarifying, smoothening +
exfoliating system

Validated
Hypoallergenic:
VH -109/109
sans all common allergens,
extended allergen series:
North American Contact Dermatitis
Group + European Surveillance
System on Contact Allergies

100% All-Types-Of-Fragrance-Free.

100% SLS + Allergen-Surfactant-Free.

100% Dye, Phthalate, Paraben + Preservative-Free.

Usage + Patch Tested.

Non-Comedogenic. Non-Drying.

For All Skin Types.

For Men + Women.

120 mL (4 Fl. Oz.) - 120 mL